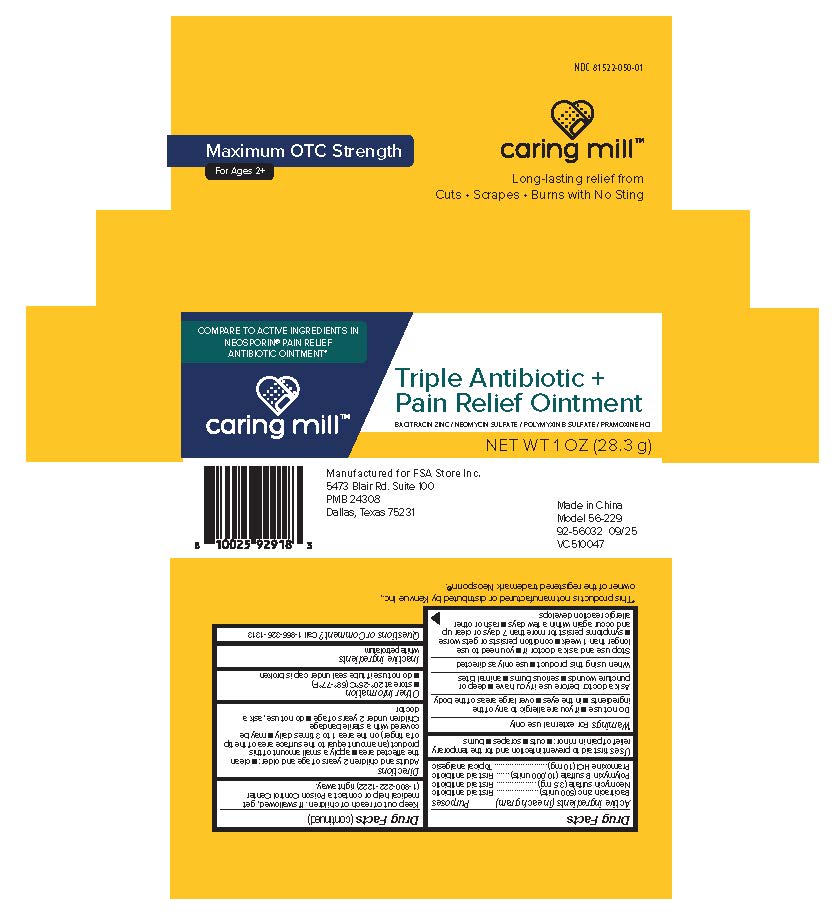 DRUG LABEL: Caring Mill Triple Antibiotic and Pain
NDC: 81522-050 | Form: OINTMENT
Manufacturer: FSA Store Inc. (Caring Mills)
Category: otc | Type: HUMAN OTC DRUG LABEL
Date: 20251229

ACTIVE INGREDIENTS: PRAMOXINE HYDROCHLORIDE 10 mg/1 g; BACITRACIN ZINC 500 [USP'U]/1 g; POLYMYXIN B SULFATE 10000 [USP'U]/1 g; NEOMYCIN SULFATE 3.5 mg/1 g
INACTIVE INGREDIENTS: WHITE PETROLATUM

Caring Mill Triple Antibiotic & Pain Relief Ointment

Active Ingredient

Bacitracin zinc (500 units)................... First aid antibiotic
Neomycin sulfate (3.5 mg) .................. First aid antibiotic
Polymyxin B sulfate (10,000 units)...... First aid antibiotic
Pramoxine HCl (10 mg)........................ Topical analgesic

Purpose

First aid antibiotic
First aid antibiotic
First aid antibiotic
Topical analgesic

Uses

First aid to prevent infection and for the temporary relief of pain in minor: ■ cuts ■ scrapes ■ burns

Warnings

For External use only

Do not use

■ if you are allergic to any of the ingredients

■ in the eyes

■ over large areas of the body

Ask a doctor before use if you have

■ deep or puncture wounds

■ serious burns

■ animal bites

When using this product

■ use only as directed

Stop use and ask a doctor if

■ you need to use longer than 1 week

■ condition persists or gets worse

■ symptoms persist for more than 7 days or clear up and occur again within a few days

■ rash or other allergic reaction develops

Keep out of reach of children

If swallowed, get medical help or contact a Poison Control Center (1-800-222-1222) right away.

Directions

Adults and children 2 years of age and older:

■ clean the affected area

■ apply a small amount of this product (an amount equal to the surface area of the tip of a finnger) on the area 1 to 3 times daily

■ may be covered with a sterile bandage Children under 2 years of age

■ do not use, ask a doctor

Other information

■ store at 20º-25ºC (68º-77ºF)
■ do not use if tube seal under cap is broken

Inactive Ingredient

white petrolatum

Questions or Comment?

Call 1-866-326-1313